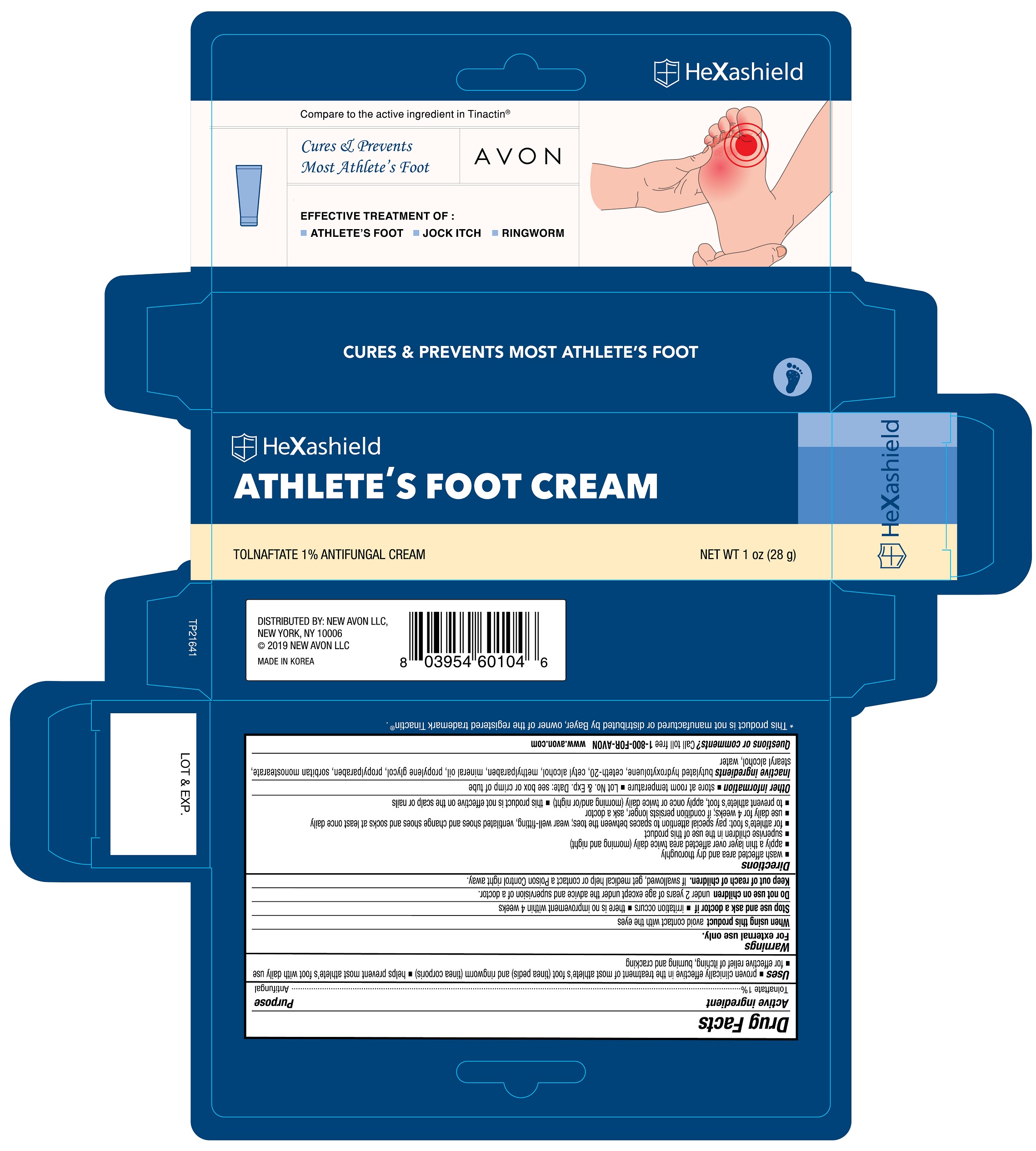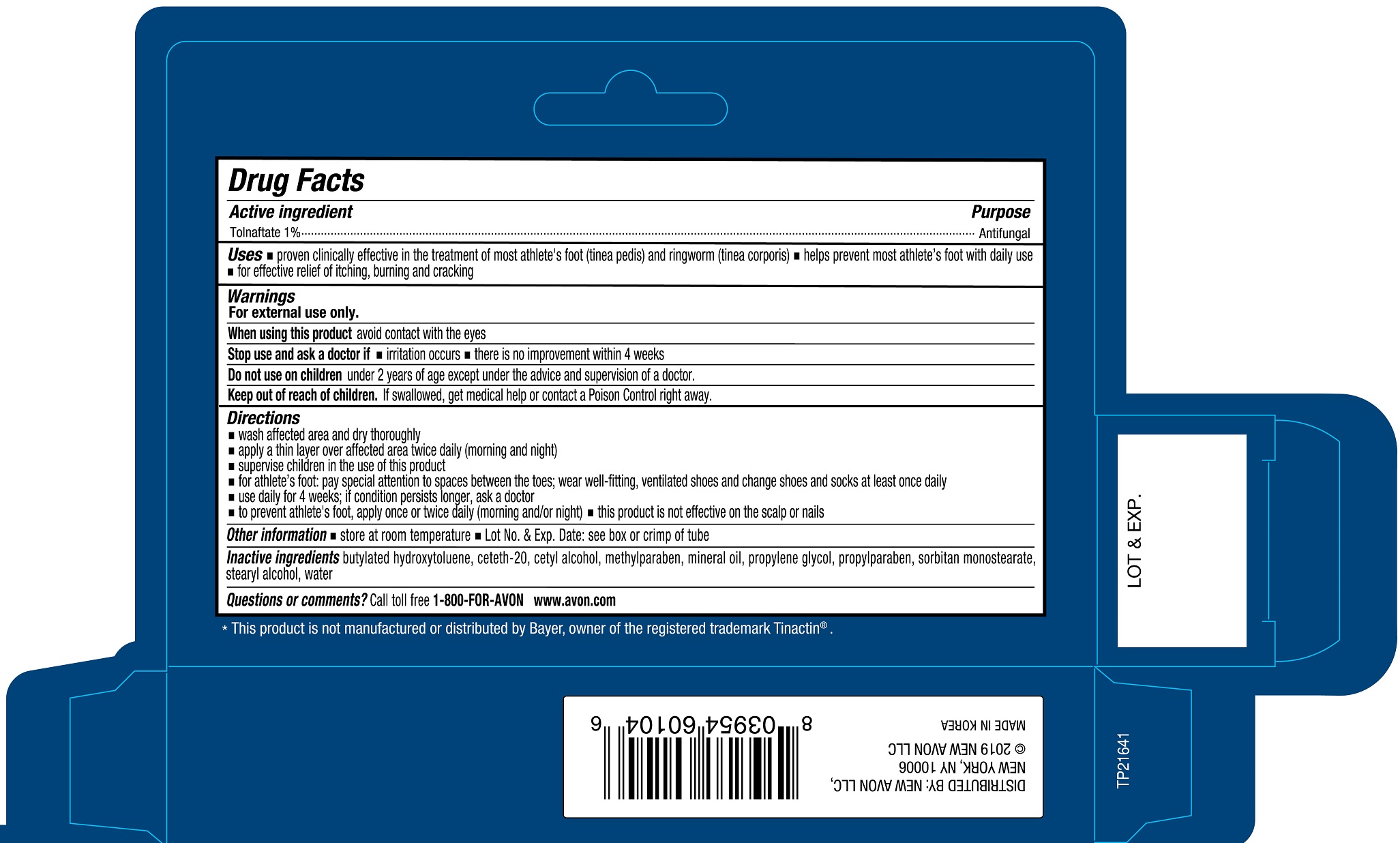 DRUG LABEL: AVON HeXashield Athletes Foot
NDC: 43136-104 | Form: CREAM
Manufacturer: Tai Guk Pharm. Co., Ltd.
Category: otc | Type: HUMAN OTC DRUG LABEL
Date: 20250101

ACTIVE INGREDIENTS: TOLNAFTATE 10 mg/1 g
INACTIVE INGREDIENTS: STEARYL ALCOHOL; WATER; BUTYLATED HYDROXYTOLUENE; SORBITAN MONOSTEARATE; CETETH-20; CETYL ALCOHOL; MINERAL OIL; METHYLPARABEN; PROPYLENE GLYCOL; PROPYLPARABEN

AVON HeXashield Althlete's Foot Cream

Active Ingredient

Tolnaftate 1 %

Purpose

Antifungal

Uses

- proven clinically effective in the treatment of most athlete's foot (tinea pedis) and ringworm (tinea corporis)
- helps prevent most athlete's foot with daily use
- for effective relief of itching, burning and cracking

Warnings

For external use only.

When using this product

- avoid contact with the eyes

Stop use and ask a doctor if :

- irritation occurs
- there is no improvement within 4 weeks

Do not use on children

- under 2 years of age except under the advice and supervision of a doctor

Keep out of reach of children.

If swallowed, get medical help or contact a Poison Control Center right away.

Directions

- wash affected area and dry thoroughly
- apply a thin layer over affected area twice daily (morning and night)
- supervise children in the use of this product
- for athlete's foot: pay special attention to spaces between the toes; wear well-fitting, ventilated shoes and change shoes and socks at least once daily
- use daily for 4 weeks; if condition persists longer, ask a doctor
- to prevent athlete's foot, apply once or twice daily (morning and night)
- this product is not effective on the scalp or nails

Other information

- store at room temperature
- Lot No. & Exp. Date: see box or crimp of tube

Inactive Ingredients

butylated hydroxytolune, ceteth-20, cetyl alcohol, methylparaben, mineral oil, propylparaben, sorbitan monostearate, stearyl alcohol, water

Questions or comments?

Call toll free 1-800-FOR-AVON

www.avon.com

Principal Display Panel

HeXasheild

Compare to the active ingredient in Tinactin®

Cures & Prevents Most Athlete's Foot

AVON

EFFECTIVE TREATMENT OF:

- ATHLETE'S FOOT - JOCK ITCH - RINGWORM

HeXashield

ATHLETE'S FOOT CREAM

TOLNAFTATE 1% ANTIFUNGAL CREAM

NET WT 1 oz (28 g)